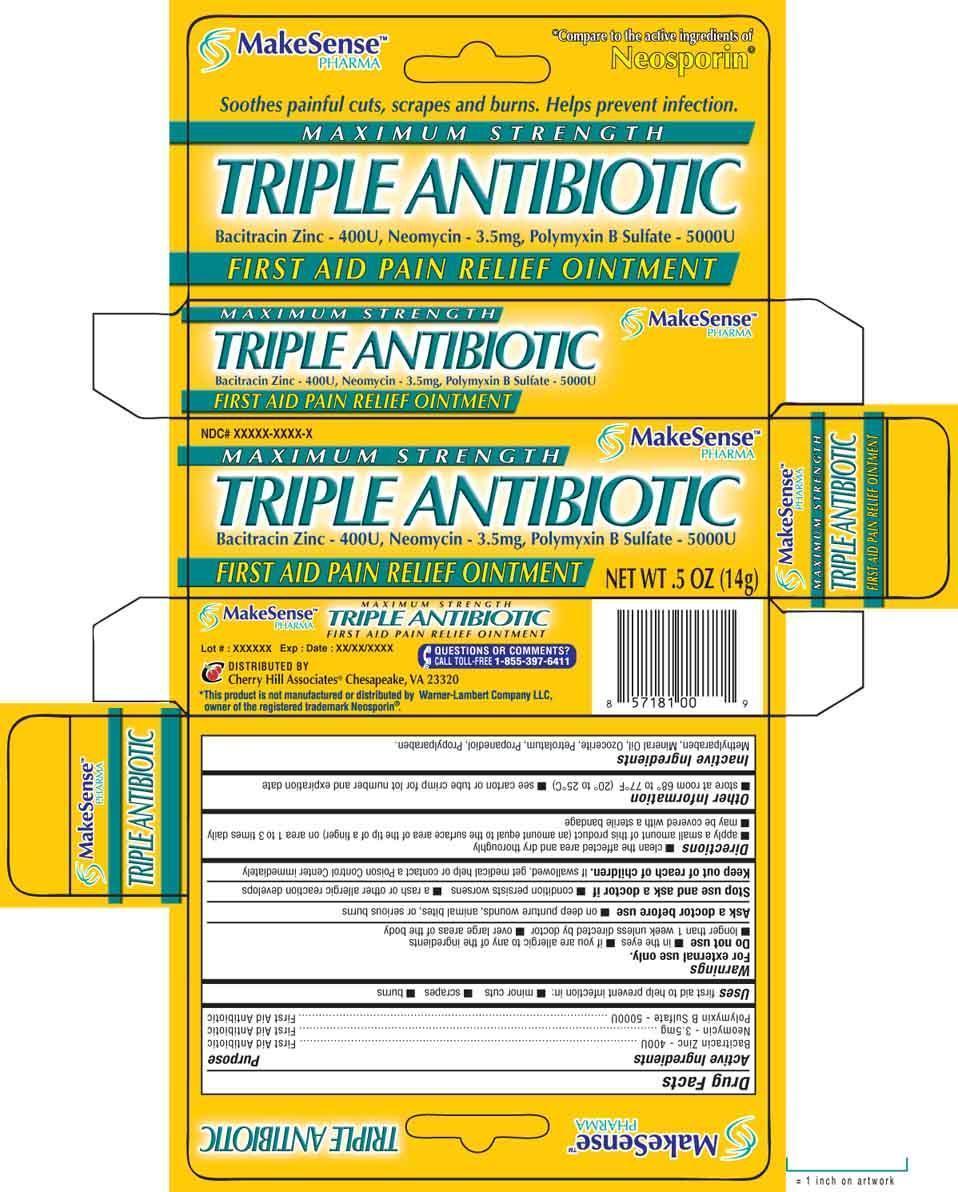 DRUG LABEL: MAKESENSE
NDC: 69020-202 | Form: OINTMENT
Manufacturer: Cherry Hill Sales Co
Category: otc | Type: HUMAN OTC DRUG LABEL
Date: 20160808

ACTIVE INGREDIENTS: BACITRACIN ZINC 400 [USP'U]/1 g; NEOMYCIN SULFATE 3.5 mg/1 g; POLYMYXIN B SULFATE 5000 [USP'U]/1 g
INACTIVE INGREDIENTS: METHYLPARABEN; MINERAL OIL; CERESIN; PETROLATUM; PROPANEDIOL; PROPYLPARABEN

Drug Facts

Active ingredients

Bacitracin Zinc 400U

Neomycin 3.5 mg

Polymyxin B sulfate 5000U

Purpose

First Aid Antibiotic

First Aid Antibiotic

First Aid Antibiotic

Uses

first aid to help prevent infection in: ■ minor cuts ■ scrapes ■ burns

Warnings

For external use only

Do not use

■ in the eyes ■ if you are allergic to any of the ingredients ■ longer than 1 week unless directed by a doctor ■ over large areas of the body

Ask a doctor before use

■ on deep puncture wounds, animal bites, or serious burns

Stop use and consult a doctor if

■ the condition persists worsens ■ a rash or other allergic reaction develops

Keep out of reach of children

If swallowed, get medical help or contact a Poison Control Center right away.

Directions

■ clean the affected area and dry thoroughly ■ apply a small amount of this product (an amount equal to the surface area of the tip of a finger) on the area 1 to 3 times daily ■ may be covered with a sterile bandage

Other Information

■ store at room temperature 68 to 77F (20to 25C) ■ see carton or tube crimp for lot number and expiration date

Inactive ingredients

Methylparaben, Mineral Oil, Ozocerite, Petrolatum, Propanediol, Propylparaben